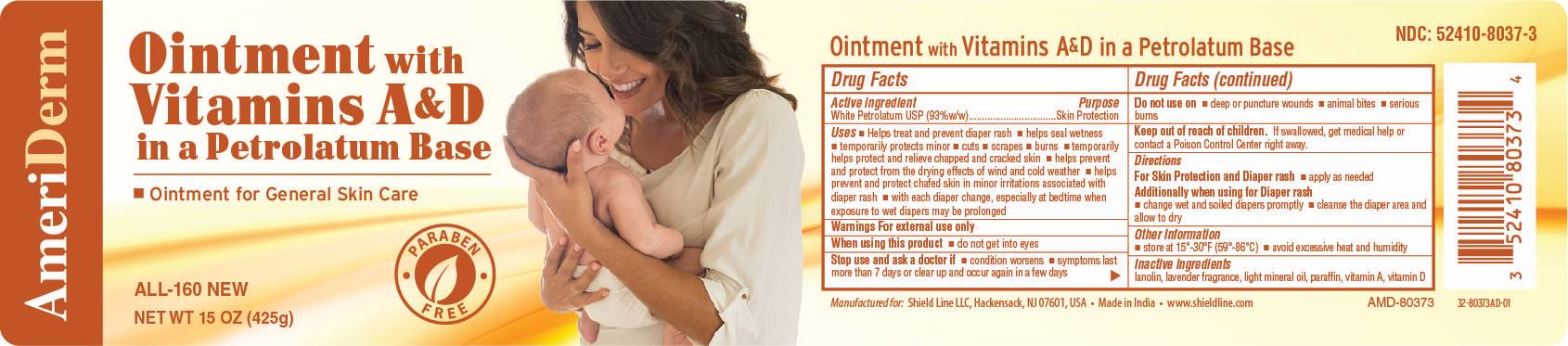 DRUG LABEL: AmeriDerm
NDC: 52410-8037 | Form: OINTMENT
Manufacturer: Shield Line LLC
Category: otc | Type: HUMAN OTC DRUG LABEL
Date: 20250815

ACTIVE INGREDIENTS: PETROLATUM 93 g/100 g
INACTIVE INGREDIENTS: LANOLIN; VITAMIN A; VITAMIN D; LIGHT MINERAL OIL; PARAFFIN

ALL-160 NEW

Active Ingredient

White petrolatum USP (93% w/w)

Purpose

Skin Protection

Uses

■ Helps treat and prevent diaper rash ■ helps seal out wetness ■ temporarily protects minor ■ cuts ■ scrapes ■ burns ■ temporarily helps protect and relieve chapped and cracked skin or lips ■ helps prevent and protect from the drying effects of wind and cold weather ■ helps prevent and protect chafed skin or minor skin irritations associated with diaper rash ■ with each diaper change, espicially at bedtime when exposure to wet diapers may be prolonged

Warnings

For external use only

When using this product

■ do not get into eyes

Stop use and ask a doctor if

■ condition worsens ■ symptoms last more than 7 days or clear up and occur again in a few days

Do not use on

■ deep or puncture wounds ■ animal bites ■ serious burns

Keep out of reach of children

If swallowed, get medical help or contact a Poison Control Center right away

Directions

For Skin Protection and Diaper rash ■ apply as needed

Additionally when using for Diaper Rash ■ change wet and soiled diapers promptly ■ cleanse the diaper area and allow to dry

Other Information

■ store at 15-30C (59-86F) ■ avoid excessive heat and humidity

Inactive ingredients

lanolin, lavender fragrance, light mineral oil, paraffin, vitamin A, vitamin D